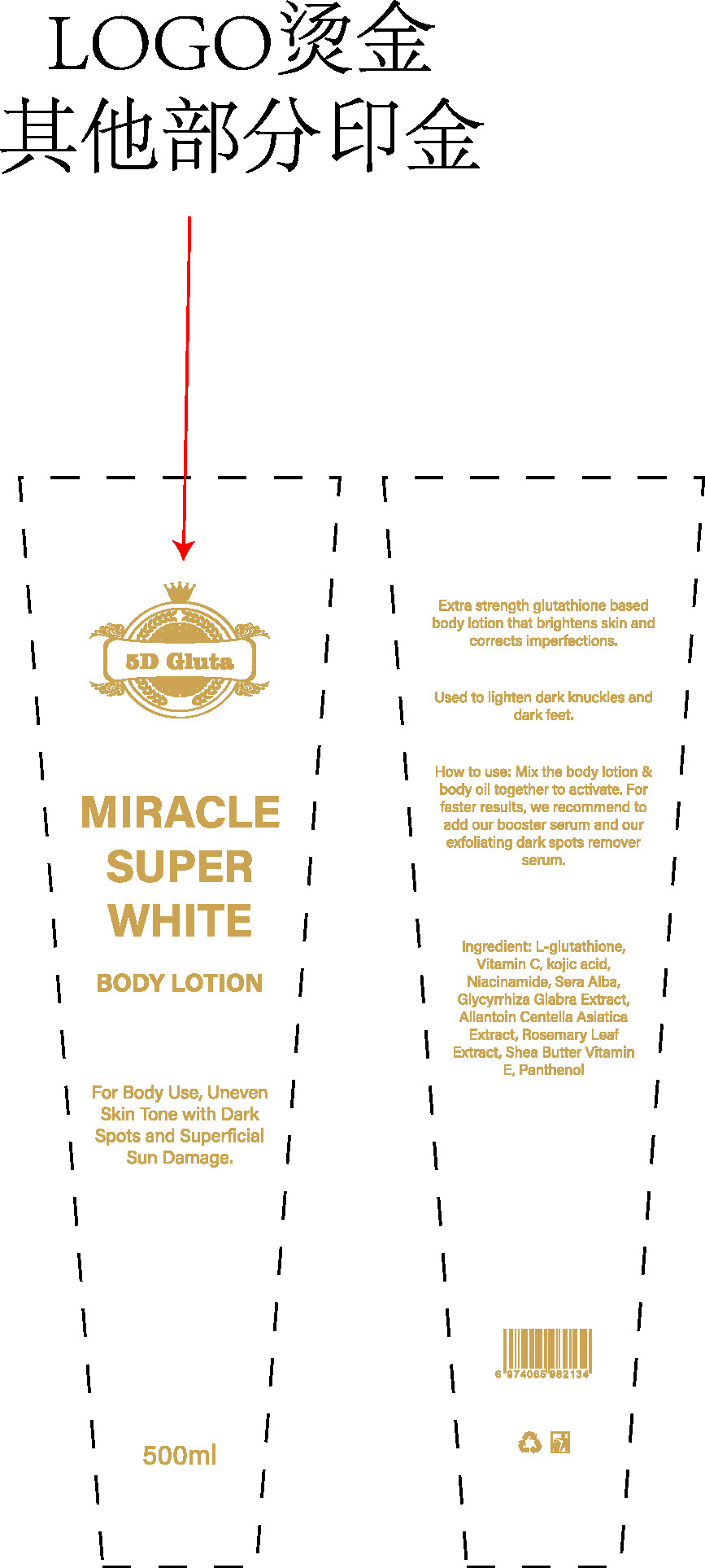 DRUG LABEL: MIRACLE SUPER WHITE BODYLOTION
NDC: 84423-031 | Form: EMULSION
Manufacturer: Guangzhou Kadiya Biotechnology Co., Ltd.
Category: otc | Type: HUMAN OTC DRUG LABEL
Date: 20240825

ACTIVE INGREDIENTS: NIACINAMIDE 10 mg/500 mL; ASCORBIC ACID 2.5 mg/500 mL; GLUTATHIONE 2.5 mg/500 mL; KOJIC ACID 4 mg/500 mL; SHEA BUTTER 10 mg/500 mL
INACTIVE INGREDIENTS: PEG-100 STEARATE; PONCEAU 4R; POTASSIUM CETYL PHOSPHATE; GLYCERYL MONOSTEARATE; TOCOPHEROL; PROPYLPARABEN; GLYCERIN; 3-O-ETHYL ASCORBIC ACID; BUTYLENE GLYCOL; SODIUM CHLORIDE; WATER; CETOSTEARYL ALCOHOL; DIMETHICONE; POLYOXYL 20 CETOSTEARYL ETHER; TROLAMINE; CARBOMER HOMOPOLYMER, UNSPECIFIED TYPE; AMARANTH; FD&C YELLOW NO. 6; UREA; EDETATE DISODIUM; FD&C BLUE NO. 1; FD&C YELLOW NO. 5; MINERAL OIL; C13-16 ISOPARAFFIN; DMDM HYDANTOIN; ALLANTOIN; METHYLPARABEN; IODOPROPYNYL BUTYLCARBAMATE

PURPOSE

Used for skin whitening

INACTIVE INGREDIENT

AQUA、MINERAL OIL、GLYCERIN、CETEARYL ALCOHOL、UREA、DIMETHICONE、GLYCERYL STEARATE、CETEARETH-20、PEG-100 STEARATE、POTASSIUM CETYL、PHOSPHATE、DMDM HYDANTOIN、TOCOPHEROL、TRIETHANOLAMINE、ALLANTOIN、CARBOMER、AROMA、METHYLPARABEN、C13-16 ISOPARAFFIN、PROPYLPARABEN、3-o-ETHYL ASCORBIC ACID、DISODIUM EDTA、CI 19140、BUTYLENE GLYCOL、IODOPROPYNYL BUTYLCARBAMATE、CI 16255、SODIUM、CHLORIDE、CI 16185、CI 15985、CI 42090

Warning.
1. Before use, perform a skin test on your arm and discontinue use if you have allergy symptoms or skin abnormalities.
2、For external use only, avoid contact with eyes when used
3、Keep out of reach of children

INDICATIONS AND USAGE

Mix the body lotion & body oil together to activate. For fester results, we recommend to add our booster serum and our exfoliating dark spots remover serum.

DOSAGE AND ADMINISTRATION

Mix the body lotion & body oil together to activate. For fester results, we recommend to add our booster serum and our exfoliating dark spots remover serum.

KEEP OUT OF REACH OF CHILDREN SECTION

Active Ingredients
NIACINAMIDE2%
GLUTATHIONE0.5%
KOJIC ACID 0.8%
ASCORBIC ACID0.5%
BUTYROSPERMUM PARKII BUTTER EXTRACT2%

PACKAGE LABEL

Active Ingredients
NIACINAMIDE2%
GLUTATHIONE0.5%
KOJIC ACID 0.8%
ASCORBIC ACID0.5%
BUTYROSPERMUM PARKII BUTTER EXTRACT2%

Uses：
Used for skin whitening
The storage method：
Store sealed in a cool place and out of sunlight

Warning.
1.Before use, perform a skin test on your arm and discontinue use if you have allergy symptoms or skin abnormalities.
2、For external use only, avoid contact with eyes when used
3、Keep out of reach of children

Inactive ingredients：
AQUA、MINERAL OIL、GLYCERIN、CETEARYL ALCOHOL、UREA、DIMETHICONE、GLYCERYL STEARATE、CETEARETH-20、PEG-100 STEARATE、POTASSIUM CETYL、PHOSPHATE、DMDM HYDANTOIN、TOCOPHEROL、TRIETHANOLAMINE、ALLANTOIN、CARBOMER、AROMA、METHYLPARABEN、C13-16 ISOPARAFFIN、PROPYLPARABEN、3-o-ETHYL ASCORBIC ACID、DISODIUM EDTA、CI 19140、BUTYLENE GLYCOL、IODOPROPYNYL BUTYLCARBAMATE、CI 16255、SODIUM、CHLORIDE、CI 16185、CI 15985、CI 42090